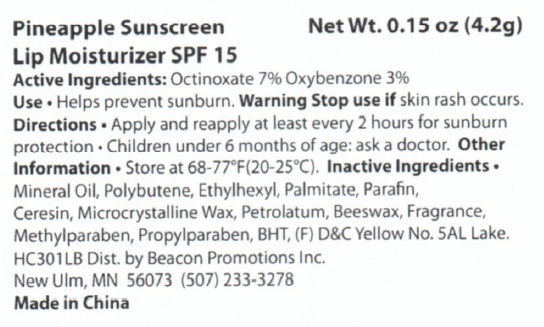 DRUG LABEL: Pineapple Sunscreen Lip Moisturizer
NDC: 75866-305 | Form: LIPSTICK
Manufacturer: Beacon Promotions, Inc.
Category: otc | Type: HUMAN OTC DRUG LABEL
Date: 20101229

ACTIVE INGREDIENTS: OCTINOXATE 7 g/100 g; OXYBENZONE 3 g/100 g
INACTIVE INGREDIENTS: MINERAL OIL; ETHYLHEXYL PALMITATE; PARAFFIN; CERESIN; MICROCRYSTALLINE WAX; PETROLATUM; YELLOW WAX; METHYLPARABEN; PROPYLPARABEN; BUTYLATED HYDROXYTOLUENE

Pineapple Sunscreen Lip Moisturizer SPF 15

Active Ingredients: Octinoxate 7%, Oxybenzone 3%

INDICATIONS AND USAGE

Use: helps prevent sunburn

WARNINGS

Warning: stop use if skin rash occurs

DOSAGE AND ADMINISTRATION

Directions: Apply and reapply at least every 2 hours for sunburn protection. children under 6 months of age: ask a doctor.

Other information: Store at 68-77F (20-25C)

Inactive Ingredients:

Mineral Oil, Polybutene, Ethylhexyl Palmitate, Parafin, Ceresin, Microcrystalline Wax, Petrolatum, Beeswax, Fragrance, Methylparaben, Propylparaben, BHT.

HC301LB Dist. by Beacon Promotions Inc.

New lm, MN 56073

(507) 233-3278

Made in China